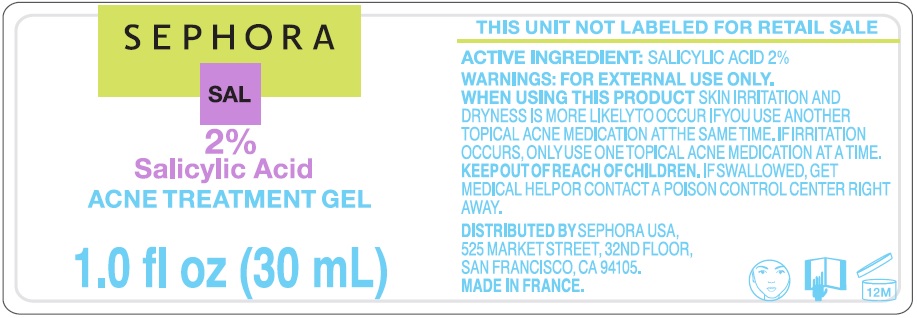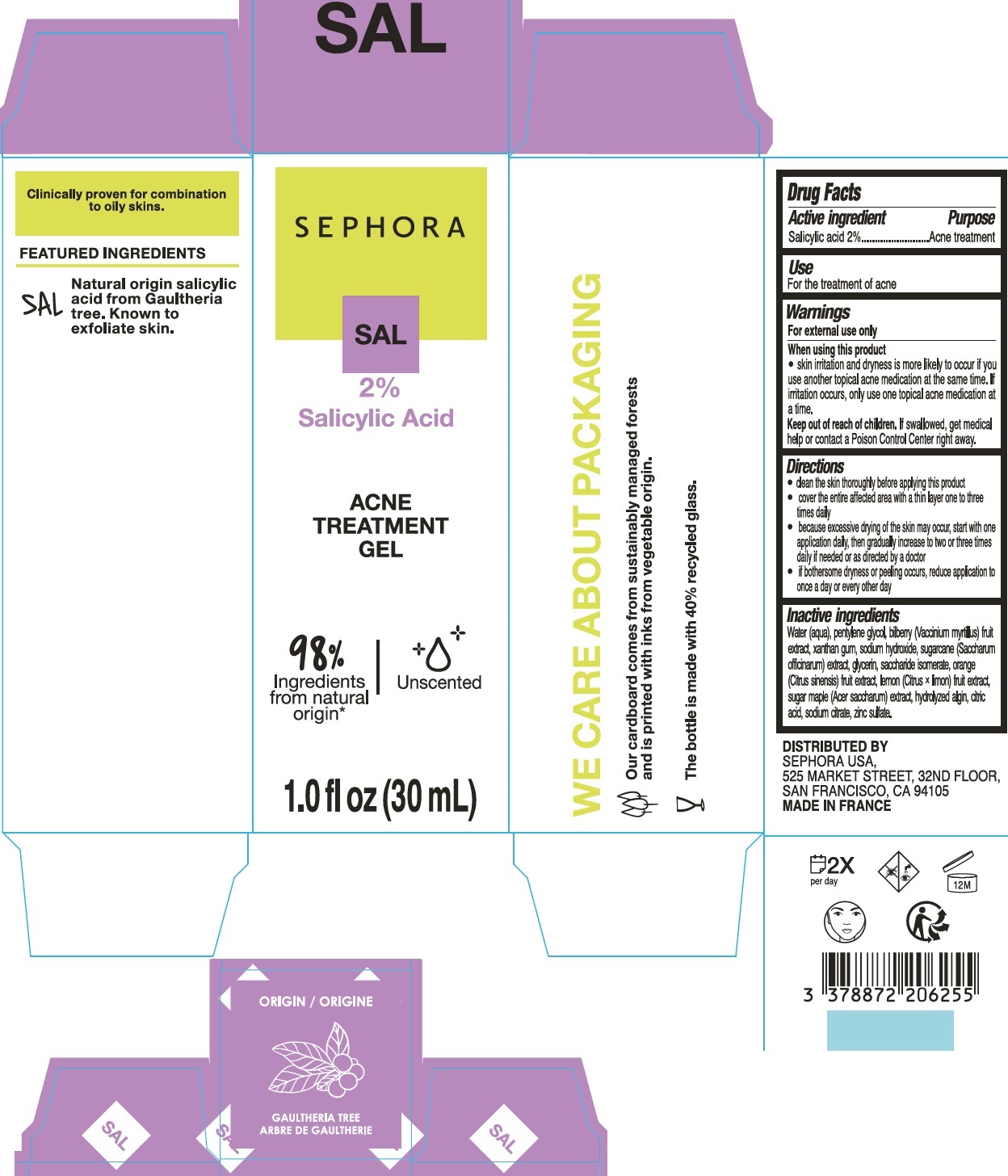 DRUG LABEL: Acne Treatment Gel
NDC: 31720-301 | Form: GEL
Manufacturer: S+
Category: otc | Type: HUMAN OTC DRUG LABEL
Date: 20251231

ACTIVE INGREDIENTS: SALICYLIC ACID 20 mg/1 mL
INACTIVE INGREDIENTS: WATER; PENTYLENE GLYCOL; MYRICA CERIFERA FRUIT; XANTHAN GUM; SODIUM HYDROXIDE; SUGARCANE; GLYCERIN; SACCHARIDE ISOMERATE; ORANGE; LEMON; CITRIC ACID MONOHYDRATE; SODIUM CITRATE; ZINC SULFATE

Acne Treatment Gel

Active ingredient

Salicylic acid 2%

Purpose

Acne treatment

Use

For the treatment of acne

Warnings

For external use only

When using this product

skin irritation and dryness is more likely to occur if you use another topical acne medication at the same time. If irritation occurs, only use one topical acne medication at a time.

Keep out of reach of children.

If swallowed, get medical help or contact a Poison Control Center right away.

Directions

- clean the skin thoroughly before applying this product
- cover the entire affected area with a thin layer one to three times daily
- because excessive drying of the skin may occur, start with one application daily, then gradually increase to two or three times daily if needed or as directed by a doctor
- if bothersome dryness or peeling occurs, reduce application to once a day or every other day

Inactive ingredients

Water (aqua), pentylene glycol, biberry (Vaccinium myrtilus) fruit extract, xanthan gum, sodium hydroxide, sugarcane (Saccharum officinarum) extract, glycerin, saccharide isomerate, orange (Citrus sinensis) fruit extract, lemon (Citrus x limon) fruit extract, sugar maple (Acer saccharum) extract, hydrolyzed algin, citric acid, sodium citrate, zinc sulfate.